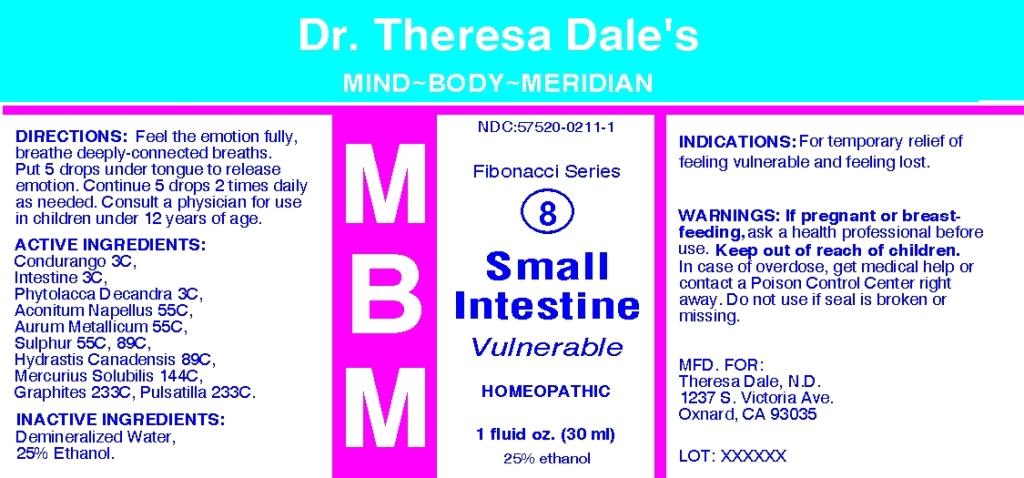 DRUG LABEL: MBM Small Intestine
NDC: 57520-0211 | Form: LIQUID
Manufacturer: Apotheca Company
Category: homeopathic | Type: HUMAN OTC DRUG LABEL
Date: 20100503

ACTIVE INGREDIENTS: PORK INTESTINE 3 [hp_C]/1 mL; PHYTOLACCA AMERICANA ROOT 3 [hp_C]/1 mL; ACONITUM NAPELLUS 55 [hp_C]/1 mL; GOLD 55 [hp_C]/1 mL; SULFUR 55 [hp_C]/1 mL; SULFUR 89 [hp_C]/1 mL; GOLDENSEAL 89 [hp_C]/1 mL; MERCURIUS SOLUBILIS 144 [hp_C]/1 mL; GRAPHITE 233 [hp_C]/1 mL; PULSATILLA VULGARIS 233 [hp_C]/1 mL; MARSDENIA CONDURANGO BARK     3 [hp_C]/1 mL
INACTIVE INGREDIENTS: WATER; ALCOHOL

MBM 8 Small Intestine

ACTIVE INGREDIENT

ACTIVE INGREDIENTS: Condurango 3C, Intestine 3C, Phytolacca decandra 3C, Aconitum napellus 55C, Aurum metallicum 55C, Sulphur 55C, 89C, Hydrastis canadensis 89C, Mercurius solubilis 144C, Graphites 233C, Pulsatilla 233C.

PURPOSE

INDICATIONS: For temporary relief of feeling vulnerable and feeling lost.

WARNINGS

WARNINGS: If pregnant or breast-feeding, ask a health professional before use. Keep out of reach of children. In case of overdose, get medical help or contact a Poison Control Center right away. Do not use if seal is broken or missing.

DOSAGE AND ADMINISTRATION

DIRECTIONS: Feel the emotion fully, breathe deeply-connected breaths. Put 5 drops under tongue to release emotion. Continue 5 drops 2 times daily as needed. Consult a physician for use in children under 12 years of age.

INACTIVE INGREDIENTS: Demineralized water, 25% Ethanol

KEEP OUT OF REACH OF CHILDREN. In case of overdose, get medical help or contact a Poison Control Center right away.

INDICATIONS AND USAGE

INDICATIONS: For temporary relief of feeling vulnerable and feeling lost.

QUESTIONS

MFD. FOR:

Theresa Dale, N.D.

1237 S. Victoria Ave.

Oxnard, CA 93035

PACKAGE LABEL

Dr. Theresa Dale's

MIND BODY MERIDIAN

NDC: 57520-0211-1

Fibonacci Series

8

MBM Small Intestine

Vulnerable

HOMEOPATHIC

1 fluid oz. (30 ml)